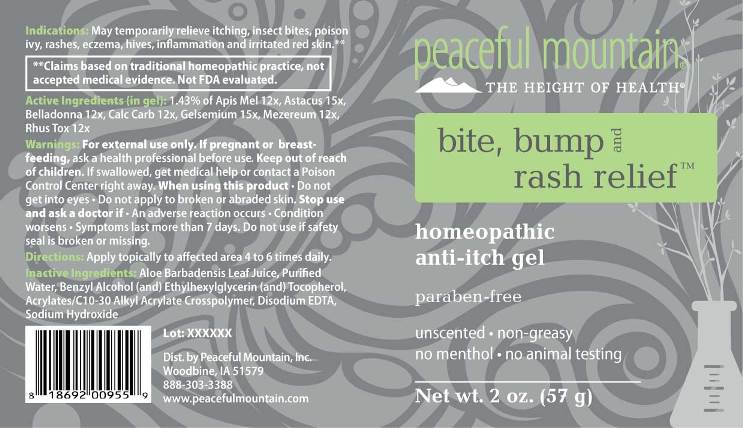 DRUG LABEL: Bite, Bump and Rash Relief
NDC: 43846-0079 | Form: GEL
Manufacturer: Peaceful Mountain, Inc.
Category: homeopathic | Type: HUMAN OTC DRUG LABEL
Date: 20250521

ACTIVE INGREDIENTS: APIS MELLIFERA 12 [hp_X]/1 g; ATROPA BELLADONNA 12 [hp_X]/1 g; OYSTER SHELL CALCIUM CARBONATE, CRUDE 12 [hp_X]/1 g; DAPHNE MEZEREUM BARK 12 [hp_X]/1 g; TOXICODENDRON PUBESCENS LEAF 12 [hp_X]/1 g; ASTACUS ASTACUS 15 [hp_X]/1 g; GELSEMIUM SEMPERVIRENS ROOT 15 [hp_X]/1 g
INACTIVE INGREDIENTS: WATER; CARBOMER INTERPOLYMER TYPE A (ALLYL SUCROSE CROSSLINKED); BENZYL ALCOHOL; ETHYLHEXYLGLYCERIN; TOCOPHEROL; SODIUM HYDROXIDE; ALOE VERA LEAF; EDETATE DISODIUM

DRUG FACTS:

ACTIVE INGREDIENTS:

(in gel): 1.43% of Apis Mellifica 12X, Astacus Fluviatilis 15X, Belladonna 12X, Calcarea Carbonica 12X, Gelsemium Sempervirens 15X, Mezereum 12X, Rhus Tox 12X.

INDICATIONS:

May temporarily relieve itching, insect bites, poison ivy, rashes, eczema, hives, inflammation and irritated red skin.**

**Claims based on traditional homeopathic practice, not accepted medical evidence. Not FDA evaluated.

WARNINGS:

For external use only.

If pregnant or breast-feeding, ask a health professional before use.

Keep out of reach of children. If swallowed, get medical help or contact a Poison Control Center right away.

When using this product • Do not get into eyes.

Stop use and ask a doctor if • Conditions worsens • Symptoms last more than 7 days

Do not use if safety seal is broken or missing.

Keep out of reach of children. If swallowed, get medical help or contact a Poison Control Center right away.

DIRECTIONS:

Apply at least 3 times daily over the affected area.

Children under 12 years of age: Consult a doctor.

INDICATIONS:

May temporarily relieve itching, insect bites, poison ivy, rashes, eczema, hives, inflammation and irritated red skin.**

**Claims based on traditional homeopathic practice, not accepted medical evidence. Not FDA evaluated.

INACTIVE INGREDIENTS:

Aloe Barbadensis Leaf Juice, Purified Water, Benzyl Alcohol (and) Ethylhexylglycerin (and) Tocopherol, Acrylates/C10-30 Alkyl Acrylate Crosspolymer, Disodium EDTA, Sodium Hydroxide (Solution).

QUESTIONS:

Dist. by Peaceful Mountain, Inc.
Woodbine, IA 51579

888-303-3388
www.peacefulmountain.com

PACKAGE LABEL DISPLAY:

peaceful mountain

THE HEIGHT OF HEALTH

bite, bump and

rash relief

homeopathic

anti-itch gel

paraben-free

unscented • non-greasy

No menthol • no animal testing

Net wt. 2 oz. (57 g)